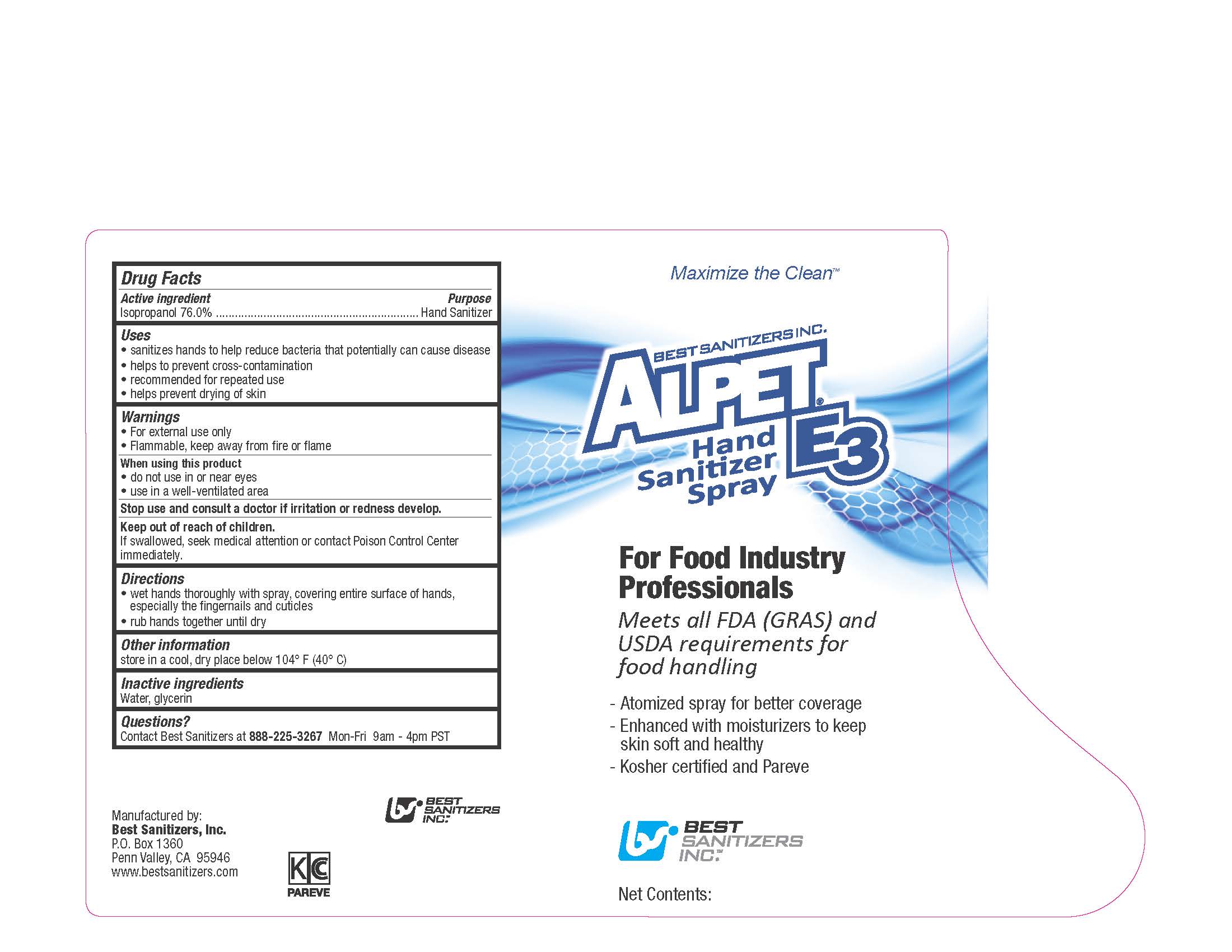 DRUG LABEL: ALPET E3 HAND SANITIZER
NDC: 59900-122 | Form: LIQUID
Manufacturer: Best Sanitizers, Inc.
Category: otc | Type: HUMAN OTC DRUG LABEL
Date: 20241205

ACTIVE INGREDIENTS: ISOPROPYL ALCOHOL 76 mL/100 mL
INACTIVE INGREDIENTS: WATER; GLYCERIN

Drug Facts 59900-122

Active ingredient

Isopropanol 76%

Purpose

Hand Sanitizer

Uses

- sanitizes hands to help reduce bacteria that potentially can cause disease

- helps to prevent cross-contamination

- recommended for repeated use

- helps prevent drying of skin

Warnings

- For external use only

- Flammable, keep away from fire or flame

When using this product

- do not use in or near eyes

- use in a well-ventilated area

Stop use and consult a doctor if irritation or redness develop.

Keep out of reach of children.

If swallowed, seek medical attention or contact Poison Control Center immediately.

Directions

- wet hands thoroughly with spray, covering entire surface of hands, especially the fingernails and cuticles

- rub hands together until dry

Other Information

store in a cool, dry place below 104oF (40oC)

Inactive ingredient

Water, glycerin

Questions?

Contact Best Sanitizers at 888-225-3267Mon-Fri 9am - 4 pm PST

PACKAGE LABEL

Maximize the Clean

BEST SANITIZERS INC.

ALPET E3

Hand

Sanitizer

Spray

For Food Industry

Professionals

Meets all FDA (GRAS) and

USDA requirements for

food handling

Atomized spray for better coverage

Enhanced with moisturizers to keep

skin soft and healthy

Kosher certified and Pareve

BEST

SANITIZERS

INC.

Net Contents: